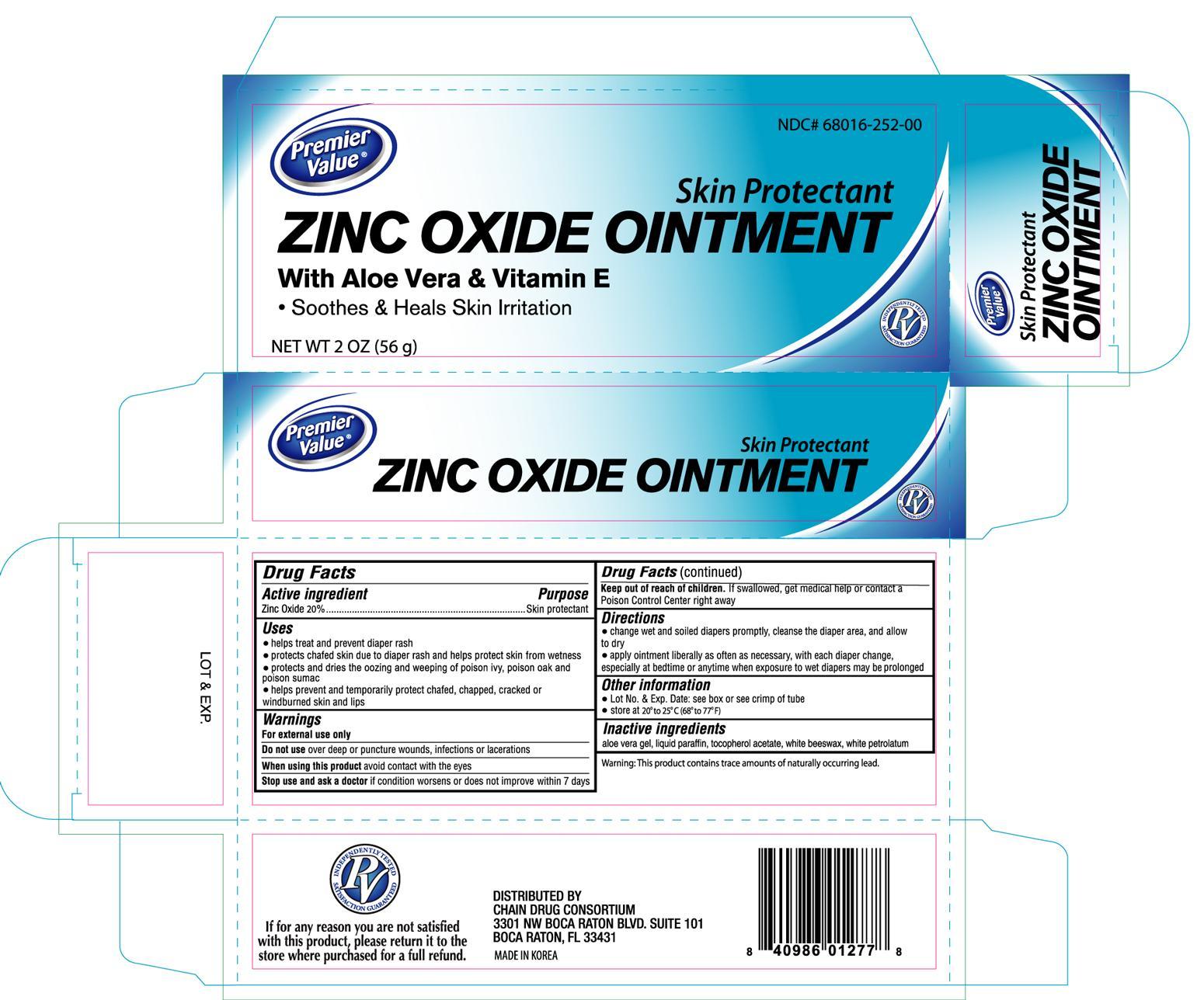 DRUG LABEL: Premier Value Zinc Oxide
NDC: 68016-252 | Form: CREAM
Manufacturer: Chain Drug Consortium, LLC
Category: otc | Type: HUMAN OTC DRUG LABEL
Date: 20130430

ACTIVE INGREDIENTS: ZINC OXIDE 20 g/100 g
INACTIVE INGREDIENTS: ALOE VERA LEAF; MINERAL OIL; ALPHA-TOCOPHEROL ACETATE; WHITE WAX; PETROLATUM

Drug Facts

Active ingredient Purpose

Zinc Oxide 20%.............................................................Skin protectant

Uses

- helps treat and prevent diaper rash
- protects chafed skin due to diaper rash and helps protect skin from wetness
- protects and dries the oozing and weeping of poison ivy, poison oak and poison sumac
- helps prevent and temporarily protect chafed, chapped, cracked or windburned skin and lips

Warnings For external use only

Do not use over deep or puncture wounds, infections or lacerations

When using this product avoid contact with the eyes

Stop use and ask a doctor if condition worsens or does not improve within 7 days

Keep out of reach of children. If swallowed, get medical help or contact a Poison Control Center right away

Directions

- change wet and soiled diapers promptly, cleanse the diaper area, and allow to dry
- apply ointment liberally as often as necessary, with each diaper change, especially at bedtime or anytime when exposure to wet diapers may be prolonged

Other information

- Lot No. and Exp. Date: see box or see crimp of tube
- store at 20° to 25°C (68° to 77°F)

INACTIVE INGREDIENT

Inactive ingredients aloe vera gel, liquid paraffin, tocopherol acetate, white beeswax, white petrolatum

DOSAGE AND ADMINISTRATION

Distributed By

Chain Drug Consortium

3301 NW Boca Raton Blvd. Suite 101

Boca Raton, FL 33431

Made in Korea